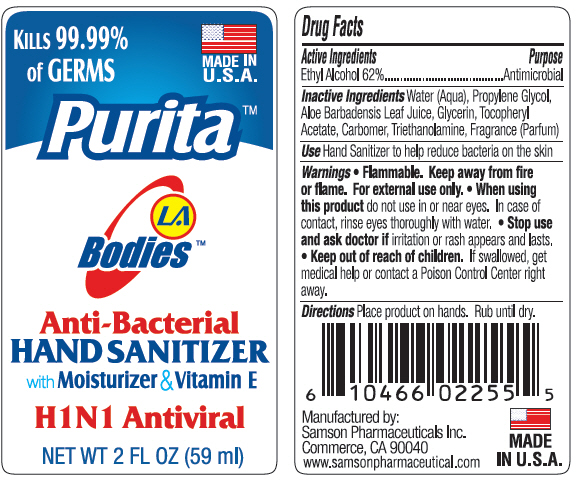 DRUG LABEL: LA Bodies Purita Anti-Bacterial Hand Sanitizer
NDC: 20146-4009 | Form: GEL
Manufacturer: SAMSON PHARMACEUTICAL
Category: otc | Type: HUMAN OTC DRUG LABEL
Date: 20220131

ACTIVE INGREDIENTS: Alcohol 620 mg/1 mL
INACTIVE INGREDIENTS: water; propylene glycol; aloe vera leaf; glycerin; .alpha.-tocopherol acetate; carbomer homopolymer type c (allyl pentaerythritol crosslinked); trolamine

LA Bodies™ Purita™ Anti-Bacterial Hand Sanitizer

Drug Facts

Active Ingredients

Ethyl Alcohol 62%

Purpose

Antimicrobial

Inactive Ingredients

Water (Aqua), Propylene Glycol, Aloe Barbadensis Leaf Juice, Glycerin, Tocopheryl Acetate, Carbomer, Triethanolamine, Fragrance (Parfum)

Use

Hand Sanitizer to help reduce bacteria on the skin

Warnings

- Flammable. Keep away from fire or flame. For external use only.
- When using this product do not use in or near eyes. In case of contact, rinse eyes thoroughly with water.
- Stop use and ask doctor if irritation or rash appears and lasts.

- Keep out of reach of children. If swallowed, get medical help or contact a Poison Control Center right away.

Directions

Place product on hands. Rub until dry.

Manufactured by:
Samson Pharmaceuticals Inc.
Commerce, CA 90040

PRINCIPAL DISPLAY PANEL - 59 ml Bottle Label

KILLS 99.99%
of GERMS

MADE IN
U.S.A.

Purita™

LA
Bodies™

Anti-Bacterial
HAND SANITIZER
with Moisturizer & Vitamin E

H1N1 Antiviral

NET WT 2 FL OZ (59 ml)